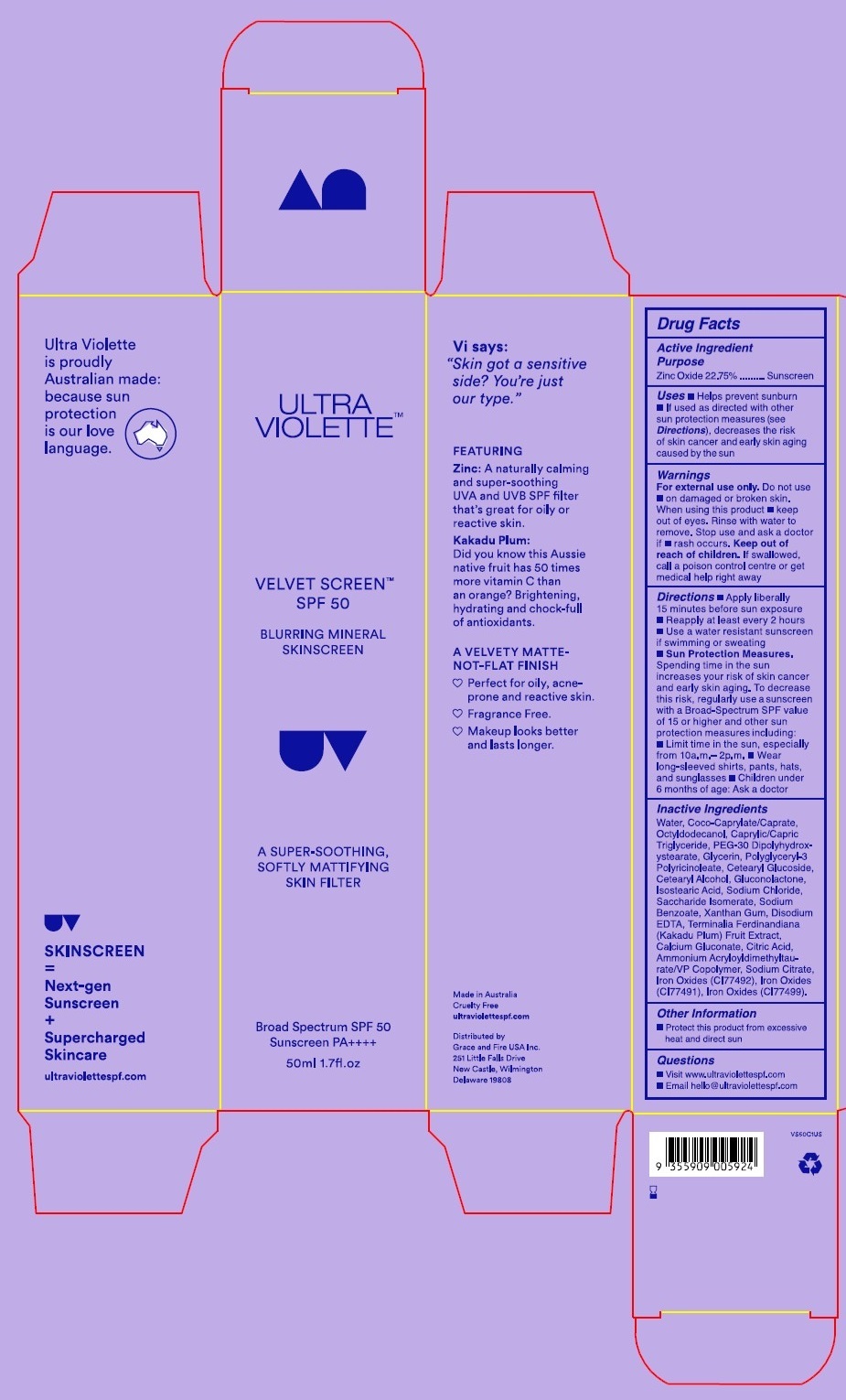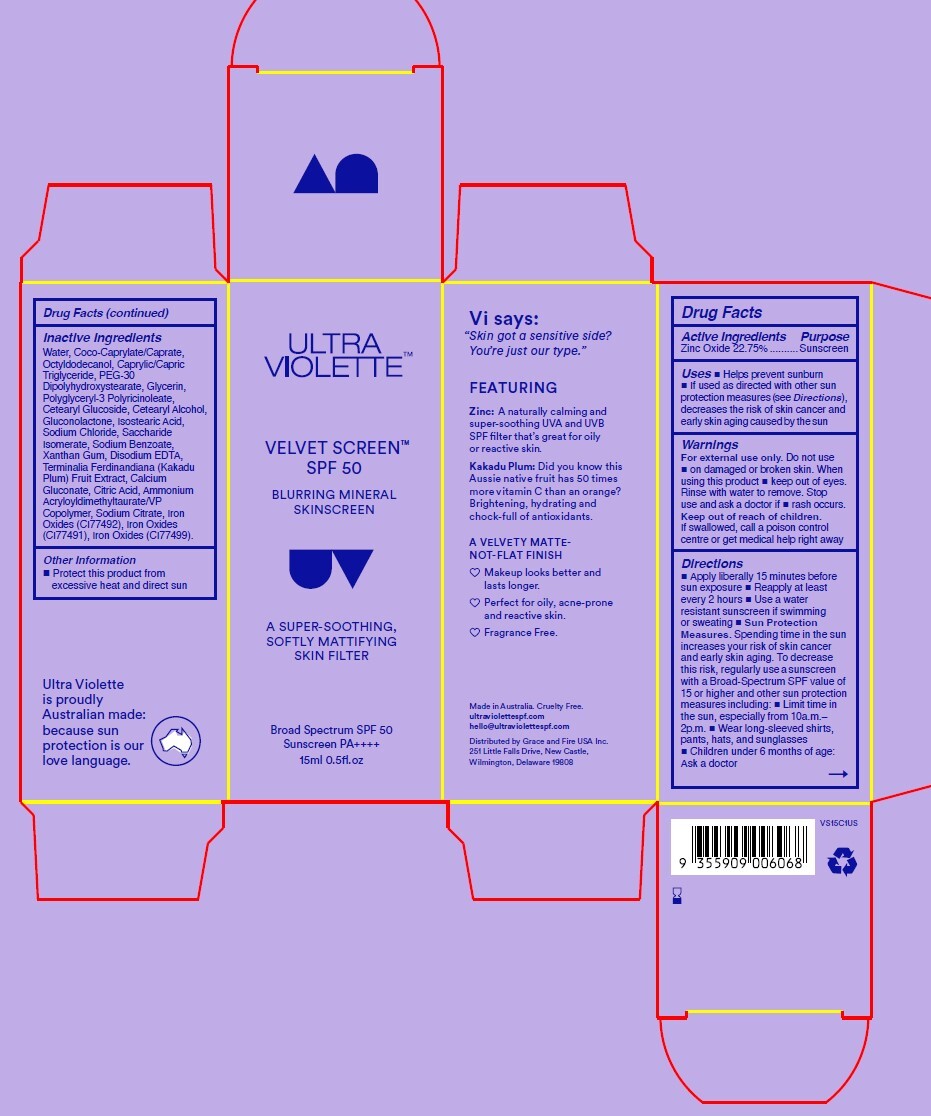 DRUG LABEL: ULTRA VIOLETTE SPF ON THE GLOW
NDC: 84803-111 | Form: KIT | Route: TOPICAL
Manufacturer: Grace And Fire USA Inc.
Category: otc | Type: HUMAN OTC DRUG LABEL
Date: 20260106

ACTIVE INGREDIENTS: OCTISALATE 50 mg/1 mL; OCTOCRYLENE 60 mg/1 mL; HOMOSALATE 100 mg/1 mL; AVOBENZONE 30 mg/1 mL; AVOBENZONE 3 g/100 g; OCTINOXATE 5 g/100 g; OCTOCRYLENE 4.7 g/100 g
INACTIVE INGREDIENTS: DIISOPROPYL ADIPATE; ASCORBYL TETRAISOPALMITATE; CAPRYLYL GLYCOL; ISODODECANE; BUTYLENE GLYCOL; .ALPHA.-TOCOPHEROL ACETATE; BENZYL SALICYLATE; HELIANTHUS ANNUUS (SUNFLOWER) SEED; ALCOHOL; ALOE BARBADENSIS LEAF; SODIUM HYALURONATE; ETHYLHEXYL PALMITATE; LINALOOL, (-)-; CAMELLIA SINENSIS LEAF OIL; NIACINAMIDE; GLYCINE MAX (SOYBEAN) OIL; HEXYL CINNAMAL; HEXYLENE GLYCOL; PHENOXYETHANOL; BISABOLOL; ACRYLATES/OCTYLACRYLAMIDE COPOLYMER (40000 MW); SILICA DIMETHYL SILYLATE; TOCOPHEROL; BUTYROSPERMUM PARKII (SHEA) BUTTER; CI 77491; RICINUS COMMUNIS (CASTOR) SEED OIL; CAPRYLIC/CAPRIC TRIGLYCERIDE; TITANIUM DIOXIDE; WHITE WAX; MYROTHAMNUS FLABELLIFOLIA TOP; THEOBROMA CACAO (COCOA) SEED BUTTER; HELIANTHUS ANNUUS (SUNFLOWER) SEED OIL; LANOLIN; OLEA EUROPAEA (OLIVE) FRUIT OIL

ULTRA VIOLETTE SPF ON THE GLOW - SPF 50 Duo Pack Kit
1 X Ultra Violette Preen Screen Broad Spectrum SPF 50
1 X Ultra Violette Sheen Screen Broad Spectrum Hydrating Lip Balm Dusk

Active Ingredients

ACTIVE INGREDIENTS : VELVET SCREEN SPF 50

ZINC OXIDE 22.75%

ACTIVE INGRDIENTS : SUPREME SCREEN SPF 50

Avobenzone 3%

Homosalate 7%

Octisalate 5%

Octocrylene 8%

Purpose

Sunscreen

Uses

Uses  Helps prevent sunburn
 If used as directed with other sun
protection measures (see Directions),
decreases the risk of skin cancer and
early skin aging caused by the sun

Warnings

For External use Only

Do not use

- on damaged or broken skin, when using this product

- keep out of eyes rinse with water to remove

Stop use and ask doctor if

- rash occur

Keep out of reach of children

if swallowed , call a poison control centre or get medical help right away

Directions

 Apply liberally 15 minutes before
sun exposure  Reapply at least
every 2 hours  Use a water
resistant sunscreen if swimming
or sweating  Sun Protection
Measures. Spending time in the sun
increases your risk of skin cancer
and early skin aging. To decrease
this risk, regularly use a sunscreen
with a Broad-Spectrum SPF value of
15 or higher and other sun protection
measures including:  Limit time in
the sun, especially from 10a.m.–
2p.m.  Wear long-sleeved shirts,
pants, hats, and sunglasses
 Children under 6 months of age:
Ask a doctor

Inactive Ingredients

Inactive Ingredients : VELVET SCREEN SPF
Water, Coco-Caprylate/Caprate,
Octyldodecanol, Caprylic/Capric
Triglyceride, PEG-30
Dipolyhydroxystearate, Glycerin,
Polyglyceryl-3 Polyricinoleate,
Cetearyl Glucoside, Cetearyl Alcohol,
Gluconolactone, Isostearic Acid,
Sodium Chloride, Saccharide
Isomerate, Sodium Benzoate,
Xanthan Gum, Disodium EDTA,
Terminalia Ferdinandiana (Kakadu
Plum) Fruit Extract, Calcium
Gluconate, Citric Acid, Ammonium
Acryloyldimethyltaurate/VP
Copolymer, Sodium Citrate, Iron
Oxides (CI77492), Iron Oxides
(CI77491), Iron Oxides (CI77499).

Inactive Ingredients : SUPREME SCREEN SPF 50
Water, Alcohol Denat., Butylene Glycol, Diisopropyl Adipate, Glycerin, Cetearyl Alcohol, Caprylyl Methicone, Isododecane, Copernicia Cerifera (Camauba) Wax, Oryza Sativa (Rice) Bran Wax, Polysorbale 60, Dimethicone, Ceteareth-20, Nylon-6/12, Saccharide Isamerate, Squalane, Camosine, Tocopheryl Acetate, Terminalia Ferdinandiana (Kakadu Plum) Fruit Extract, Silica, PEG-40 Stearate, Citric Acid, Hydroxyelnyl Acrlale/Sodiumm
Acryloyloimelnyl Taurale Copolymer, Glyceryl Capryllate, Fragrance, Disodium EDTA, Pentylene Clyool, Caprylhydraxamio Acid,
Triethanolamino, Laotic Aoid, Sorbitan Isostearate, Sodium Citrate, Iron Oxides (C| 77491), Iron Oxides (C|77492), Iron Oxides (C| 77499).

Other Information

Protect this product from excessive heat and direct sun

Broad Spectrum SPF 50
Sunscreen PA++++
15ml